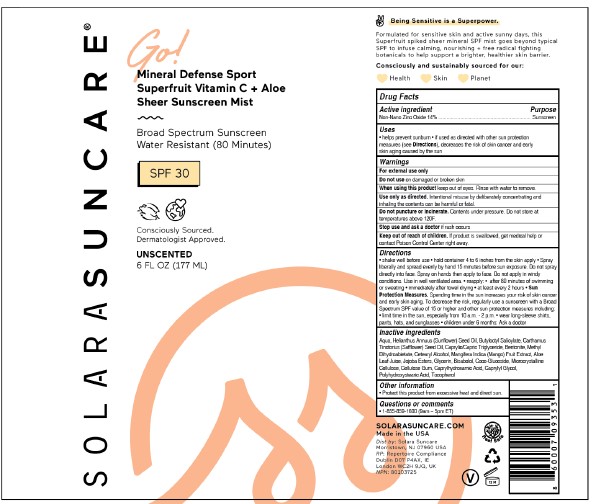 DRUG LABEL: SOLARA SUNCARE - GO MINERAL DEFENSE SPORT SUPERFRUIT VITAMIN C PLUS ALOE SHEER SUNSCREEN MIST

NDC: 73054-109 | Form: SPRAY
Manufacturer: SOLARA SUNCARE, INC.
Category: otc | Type: HUMAN OTC DRUG LABEL
Date: 20251222

ACTIVE INGREDIENTS: ZINC OXIDE 14 g/100 mL
INACTIVE INGREDIENTS: WATER; MEDIUM-CHAIN TRIGLYCERIDES; GLYCERIN; SUNFLOWER OIL; TOCOPHEROL; BUTYLOCTYL SALICYLATE; SAFFLOWER OIL; BENTONITE; METHYL DIHYDROABIETATE; CETOSTEARYL ALCOHOL; MANGO; ALOE VERA LEAF; HYDROGENATED JOJOBA OIL/JOJOBA OIL, RANDOMIZED (IODINE VALUE 40-44); LEVOMENOL; COCO GLUCOSIDE; CAPRYLYL GLYCOL; MICROCRYSTALLINE CELLULOSE; CARBOXYMETHYLCELLULOSE SODIUM, UNSPECIFIED FORM; CAPRYLHYDROXAMIC ACID; POLYHYDROXYSTEARIC ACID (2300 MW)

SOLARA (as PLD) - GO! MINERAL DEFENSE SPORT SUPERFRUIT VITAMIN C + ALOE SHEER SUNSCREEN MIST (73054-109)

ACTIVE INGREDIENTS

Non-Nano, Non-Coated Zinc Oxide 14%

PURPOSE

Sunscreen

USES

- helps prevent sunburn
- if used as directed with other sun protection measures (see Directions), decreases the risk of skin cancer and early skin aging caused by the sun

WARNINGS

For external use only

Do not use on damaged or broken skin

When using this product keep out of eyes. Rinse with water to remove.

Use only as directed. Intentional misuse by deliberately concentrating and inhaling the contents can be harmful or fatal.

Do not puncture or incinerate. Contents under pressure. Do not store at temperatures above 120F.

Stop use and ask a doctor if rash occurs

Keep out of reach of children. If product is swallowed, get medical help or contact Poison Control Center right away.

DIRECTIONS

- shake well before use
- hold container 4 to 6 inches from the skinapply
- Spray liberally and speard evenly by hand 15 minutes before sun exposure. Do not spray directly into face. Spray on hands then apply to face. Do not apply in windy conditions. Use in a well ventilated area.

- reapply:
- after 80 minutes of swimming or sweating
- immediately after towel drying
- at least every 2 hours

- Sun Protection Measures. Spending time in the sun increases your risk of skin cancer and early skin aging. To decrease the risk, regularly use asunscreen with a Broad Spectrum SPF value of 15 or higher and other sun protection measures including:
- limit time in the sun, especially from 10 a.m. - 2 p.m.
- wear long-sleeve shirts, pants, hats, and sunglasses
- children under 6 months: Ask a doctor

INACTIVE INGREDIENTS

AQUA, HELIANTHUS ANNUUS (SUNFLOWER) SEED OIL, BUTYLOCTYL SALICYLATE, CARTHAMUS TINCTORIUS (SAFFLOWER) SEED OIL, CAPRYLIC/CAPRIC TRIGLYCERIDE, BENTONITE, METHYL DIHYDROABIETATE, CETEARYL ALCOHOL, MANGIFERA INDICA (MANGO) FRUIT EXTRACT, ALOE LEAF JUICE, JOJOBA ESTERS, GLYCERIN, BISABOLOL, COCO-GLUCOSIDE, MICROCRYSTALLINE CELLULOSE, CELLULOSE GUM, CAPRYLHYDROXAMIC ACID, CAPRYLYL GLYCOL, POLYHYDROXYSTEARIC ACID, TOCOPHEROL

OTHER INFORMATION

- Protect this product from excessive heat and direct sun.

QUESTIONS OR COMMENTS

- 1-855-859-1600 (9am – 5pm ET)